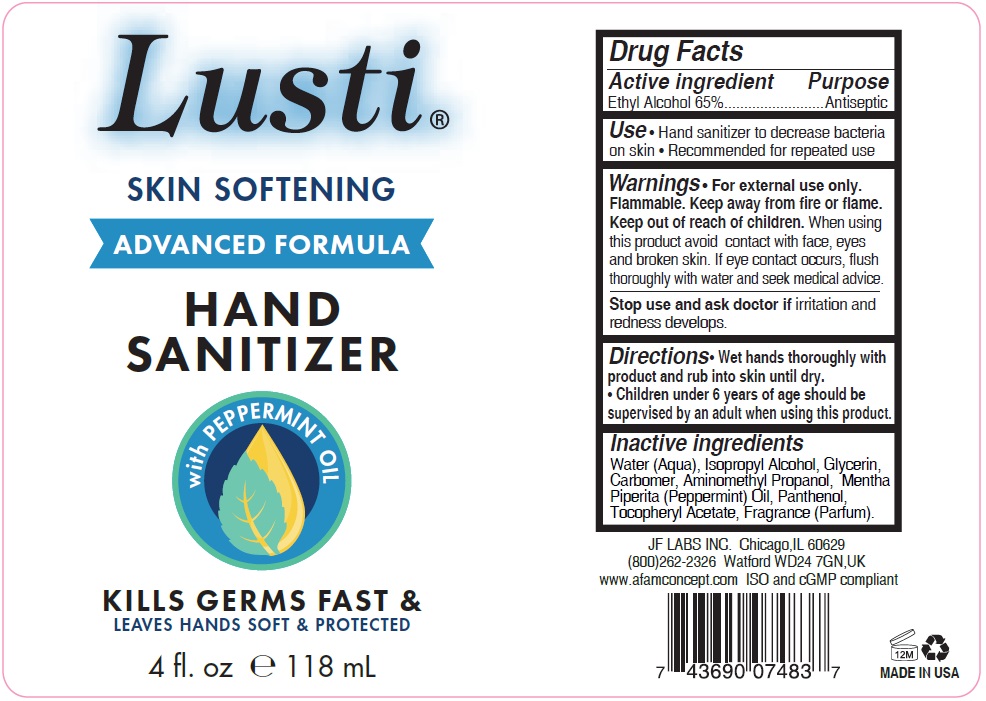 DRUG LABEL: LUSTI Skin Softening hand sanitizer
NDC: 49681-400 | Form: LIQUID
Manufacturer: New Life Products, Inc.
Category: otc | Type: HUMAN OTC DRUG LABEL
Date: 20230202

ACTIVE INGREDIENTS: ALCOHOL 65 mL/100 mL
INACTIVE INGREDIENTS: WATER; ISOPROPYL ALCOHOL; GLYCERIN; CARBOMER HOMOPOLYMER, UNSPECIFIED TYPE; AMINOMETHYLPROPANOL; PEPPERMINT OIL; PANTHENOL; .ALPHA.-TOCOPHEROL ACETATE

Lusti® SKIN SOFTENING HAND SANITIZER

Active ingredient

Ethyl Alcohol 65%

Purpose

Antiseptic

INDICATIONS AND USAGE

Use • Hand sanitizer to decrease bacteria on skin • Recommended for repeated use

Warnings • For external use only. Flammable.

Keep away from fire or flame.

When using this product avoid contact with face, eyes and broken skin. If eye contact occurs, flush thoroughly with water and seek medical advice.

Stop use and ask a doctor if irritation and redness develops.

Keep out of reach of children

DOSAGE AND ADMINISTRATION

Directions• Wet hands thoroughly with product and rub into skin until dry.

• Children under 6 years of age should be supervised by an adult when using this product

Inactive ingredients

Water (Aqua), Isopropyl Alcohol, Glycerin, Carbomer, Aminomethyl Propanol, Mentha Piperita (Peppermint) Oil, Panthenol, Tocopheryl Acetate, Fragrance(Parfum).

ADVANCED FORMULA

with PEPPERMINT OIL

KILLS GERMS FAST &

LEAVES HANDS SOFT & PROTECTED

JF LABS INC. Chicago,IL 60629

(800)262-2326 Watford WD247GN, UK

www.afamconcept.com ISO and cGMP compliant

MADE IN USA